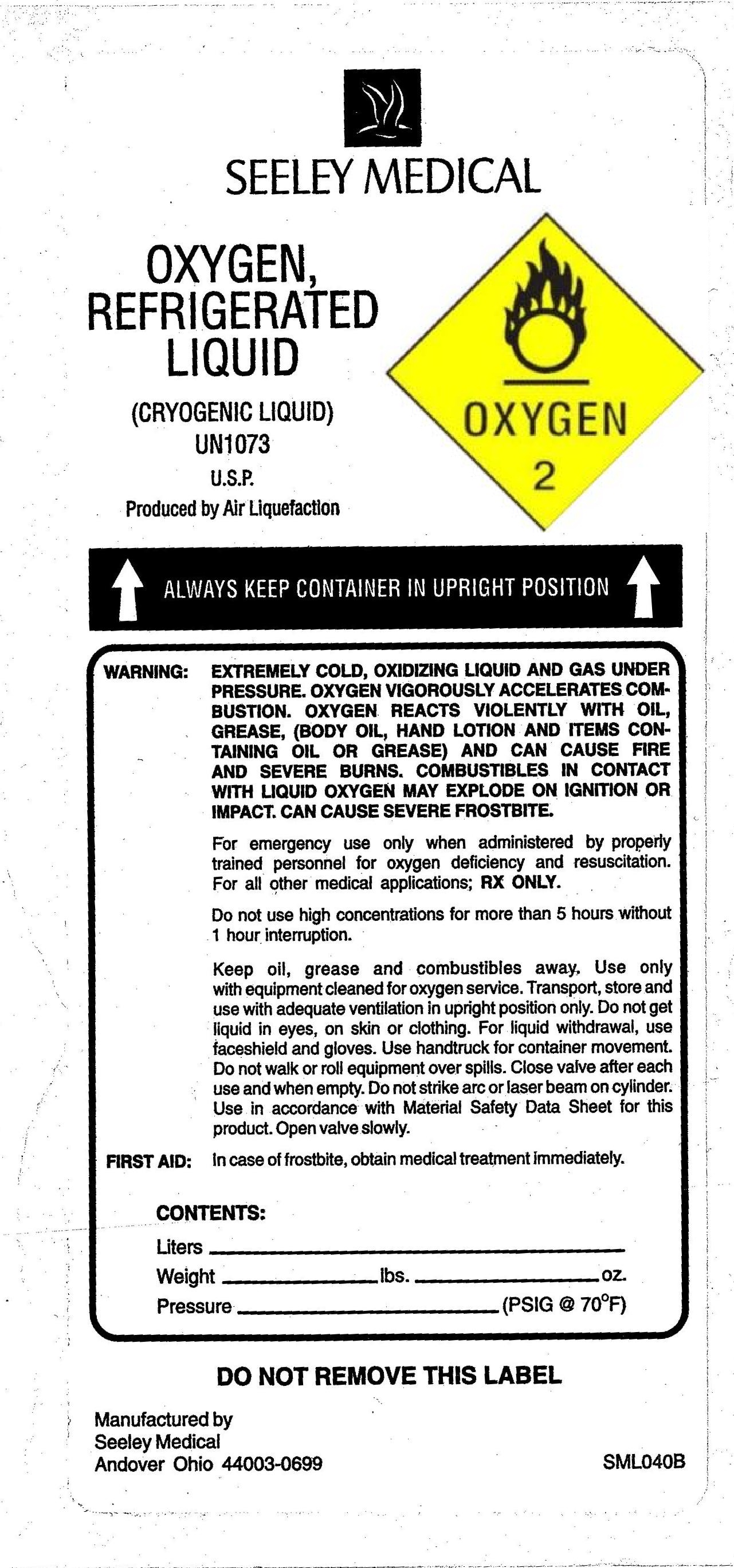 DRUG LABEL: Oxygen
NDC: 49854-001 | Form: GAS
Manufacturer: Seeley Enterprises Inc
Category: prescription | Type: HUMAN PRESCRIPTION DRUG LABEL
Date: 20101112

ACTIVE INGREDIENTS: Oxygen 999 mL/1 L

Oxygen Label

PACKAGE LABEL

SEELY MEDICAL
OXYGEN, REFRIGERATED LIQUID (CRYOGENIC LIQUID) UN1073 U.S.P. Produced by Air Liquefaction
OXYGEN 2
ALWAYS KEEP CONTAINER IN UPRIGHT POSITION
WARNING: EXTREMELY COLD, OXIDIZING LIQUID AND GAS UNDER PRESSURE. VIGOROUSLY ACCELERATES COMBUSTION. OXYGEN VIGOROUSLY ACCELERATES COMBUSTION. OXYGEN REACTS VIOLENTLY WITH OIL, GREASE, (BODY OIL, HAND LOTION AND ITEMS CONTAINING OIL OR GREASE) AND CAN CAUSE FIRE AND SEVERE BURNS. COMBUSTIBLES IN CONTACT WITH LIQUID OXYGEN MAY EXPLODE ON IGNITION OR IMPACT. CAN CAUSE SEVERE FROSTBITE.
For emergency use only when administered by properly trained personnel for oxygen deficiency and resuscitation. For all other medical applications; Rx Only.
Do not use high concentrations for more than 5 hours without 1 hour interruption.
Keep oil, grease, and combustibles away. Use only with equipment cleaned for oxygen service. Transport, store and use with adequate ventilation in upright position only. Do not get liquid in eyes, on skin, or clothing. For liquid withdrawal, use faceshield and gloves. Use hand truck for container movement. Do not walk or roll equipment over spills. Close valve after each use and when empty. Do not strike arc or laser beam on cylinder. Use in accordance with the Material Safety Data Sheet for this product. Open valve slowly. FIRST AID: IN CASE OF FROSTBITE, obtain medical treatment immediately.
CONTENTS:
Liters Weight lbs oz Pressure (PSIG @ 70F)
DO NOT REMOVE THIS LABEL.
Manufactured by Seely Medical Andover Ohio 44003-0699
SML040B